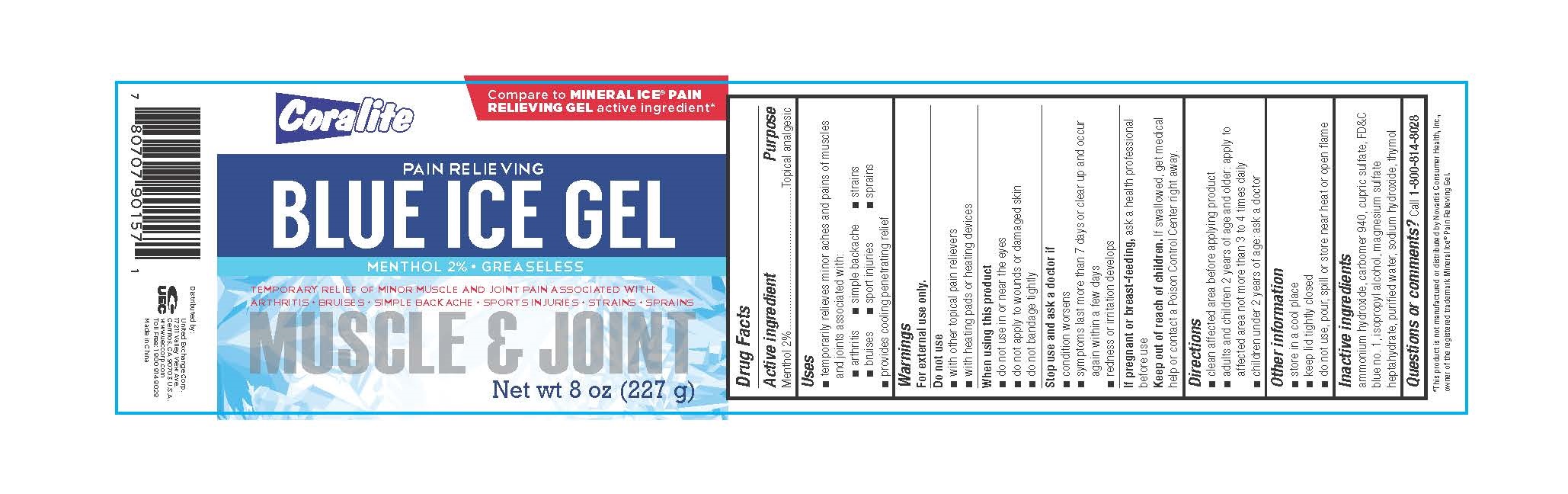 DRUG LABEL: Coralite Blue Ice
NDC: 65923-157 | Form: GEL
Manufacturer: United Exchange Corp.
Category: otc | Type: HUMAN OTC DRUG LABEL
Date: 20161005

ACTIVE INGREDIENTS: MENTHOL .02 g/1 g
INACTIVE INGREDIENTS: AMMONIA; CARBOMER 940; CUPRIC SULFATE; FD&C BLUE NO. 1; ISOPROPYL ALCOHOL; MAGNESIUM SULFATE HEPTAHYDRATE; WATER; SODIUM HYDROXIDE; THYMOL

Active ingredient Purpose

Menthol 2%........................................................Topical analgesic

Uses

- temporarily relieves minor aches and pains of muscles and joints associated with:
- arthritis
- simple backache
- strains
- bruises
- sport injuries
- sprains
- provides cooling penetrating relief

Warnings

For external use only

Do not use

- with other topical pain relievers
- with heating pads or heating devices

When using this product

- do not use in or near the eyes
- do not apply to wounds or damaged skin
- do not bandage tightly

Stop use and ask a doctor if

- condition worsens
- symptoms last more than 7 days or clear up and occur again within a few days
- redness or irritation develops

PREGNANCY OR BREAST FEEDING

If pregnant or breast-feeding, ask a health professional before use

Keep out of reach of children. If swallowed, get medical help or contact a Poison Control Center right away.

Directions

- Clean affected area before applying product
- adults and children 2 years of age and older: apply to affected area not more than 3 to 4 times daily
- children under 2 years of age: ask a doctor

Other information

- store in a cool place
- keep lid tightly closed
- do not use, pour, spill or store near heat or open flame

Inactive ingredients

ammonium hydroxide, carbomer 940, cupric sulfate, FD&C blue no. 1, isopropyl alcohol, magnesium sulfate heptahydrate, purified water, sodium hydroxide, thymol

DOSAGE AND ADMINISTRATION

Distributed by:

United Exchange Corp.

17211 Valley View Ave.

Cerritos, CA 90703 U.S.A.

www.ueccorp.com

Toll Free: 1 800 814 8028

Made in China